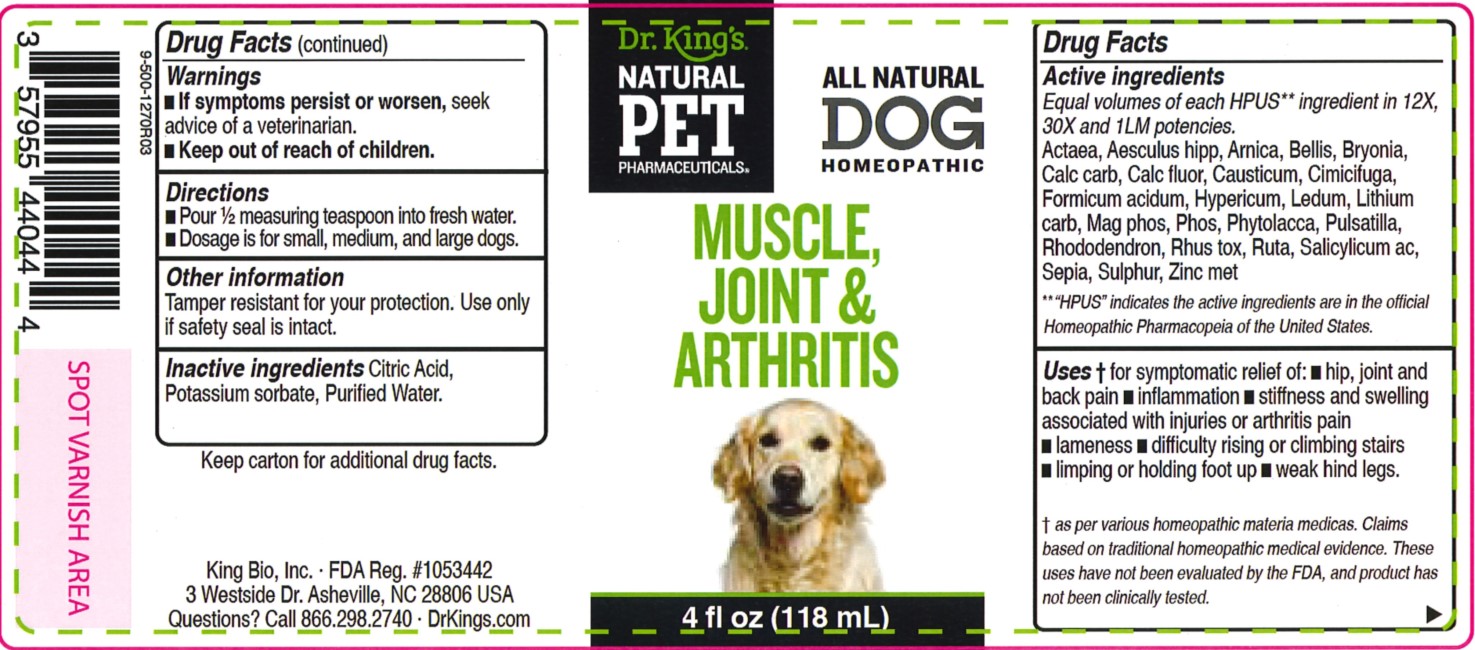 DRUG LABEL: Muscle, Joint and Arthritis
NDC: 57955-4804 | Form: LIQUID
Manufacturer: King Bio Inc.
Category: homeopathic | Type: OTC ANIMAL DRUG LABEL
Date: 20240604

ACTIVE INGREDIENTS: ACTAEA SPICATA ROOT 12 [hp_X]/118 mL; HORSE CHESTNUT 12 [hp_X]/118 mL; ARNICA MONTANA WHOLE 12 [hp_X]/118 mL; BELLIS PERENNIS WHOLE 12 [hp_X]/118 mL; BRYONIA ALBA ROOT 12 [hp_X]/118 mL; OYSTER SHELL CALCIUM CARBONATE, CRUDE 12 [hp_X]/118 mL; CALCIUM FLUORIDE 12 [hp_X]/118 mL; CAUSTICUM 12 [hp_X]/118 mL; BLACK COHOSH 12 [hp_X]/118 mL; FORMIC ACID 12 [hp_X]/118 mL; HYPERICUM PERFORATUM WHOLE 12 [hp_X]/118 mL; RHODODENDRON TOMENTOSUM LEAFY TWIG 12 [hp_X]/118 mL; LITHIUM CARBONATE 12 [hp_X]/118 mL; MAGNESIUM PHOSPHATE, DIBASIC TRIHYDRATE 12 [hp_X]/118 mL; PHOSPHORUS 12 [hp_X]/118 mL; PHYTOLACCA AMERICANA ROOT 12 [hp_X]/118 mL; PULSATILLA VULGARIS WHOLE 12 [hp_X]/118 mL; RHODODENDRON AUREUM LEAF 12 [hp_X]/118 mL; TOXICODENDRON PUBESCENS LEAF 12 [hp_X]/118 mL; RUTA GRAVEOLENS FLOWERING TOP 12 [hp_X]/118 mL; SALICYLIC ACID 12 [hp_X]/118 mL; SEPIA OFFICINALIS JUICE 12 [hp_X]/118 mL; SULFUR 12 [hp_X]/118 mL; ZINC 12 [hp_X]/118 mL
INACTIVE INGREDIENTS: CITRIC ACID MONOHYDRATE; POTASSIUM SORBATE; WATER

Muscle, Joint and Arthritis

Warnings

- If symptoms persist or worsen, seek advice of a veterinarian.
- Keep out of reach of children.

Reference image:

Directions

- Pour 1/2 measuring teaspoon into fresh water.
- Dosage is for small, medium, and large dogs.

Reference image:

Other Information

Tamper resistant for your protection.

Use only if safety seal is intact.

Keep carton for complete drug facts and product information.

This product has not been clinically tested.

Questions? Call 866.298.2740

King Bio, Inc. 3 Westside Drive

Asheville, NC, 28806 USA

FDA Reg. #1053442

For latest product information and instructions: www.DrKings.com

Keep out of reach of children.

Active Ingredients

Actaea spicata, Aesculus hippocastanum, Arnica montana, Bellis perennis, Bryonia, Calcarea carbonica, Calcarea fluorica, Causticum, Cimicifuga racemosa, Formicum acidum, Hypericum perforatum, Ledum palustre, Lithium carbonicum, Magnesia phosphorica, Phosphorus, Phytolacca decandra, Pulsatilla, Rhododendron chrysanthum, Rhus tox, Ruta graveolens, Salicylicum acidum, Sepia, Sulphur, and Zincum metallicum.

Uses

Uses of symptomatic relief of:

- inflammation
- hip, joint and back pain
- stiffness and swelling associated with injuries or arthritis pain
- lameness
- difficulty rising or climbing stairs
- limping or holing foot up
- weak hind legs

As per various homeopathic materia medicas. Claims based on traditional homeopathic pracice, not accepted medical evidence. These uses have not been evaluated be the FDA, and Product has not been clinically tested.

Inactive Ingredient

Citric acid, Potassium sorbate, and Purified water.

PURPOSE

Equal volumes of each HPUS ingredient in 12X, 30X, and 1LM potencies.

Actaea spicata............................rheumatism, joint swellings

Aesculus hippocastanum......................................sore limbs

Arnica montana........................................sprains, soreness

Bellis perennis................................sore muscles, sore joints

Bryonia.......................................................aching muscles

Calcarea carbonica...........................weakness in extremities

Calcarea fluorica.............................................pain in bones

Causticum..............................................swollen, stiff joints

Cimicifuga racemosa................................rheumatic stiffness

Formicum acidum.................................muscle and joint pain

Hypericum perforatum....................................bruised joints

Ledum palustre...........................................................pain

Lithium carbonicum.............................................sore body

Magnesia phosphorica..................................muscle spasms

Phosphorus........................................weak back and joints

Phytolacca decandra.......................................inflammation

Pulsatilla.....................................restlessness, pain in limbs

Rhododendron chrysanthum.............................................

...................................rheumatic pain and gouty symptoms

Rhus tox.....................................................rheumatic pain

Ruta graveolens........................................deposits in joints

Salicylicum acidum.............................swollen, painful knees

Sepia........................................stiff, lame, or twitching legs

Sulphur.................................................trembling, stiffness

Zincum metallicum...................................twitching muscles